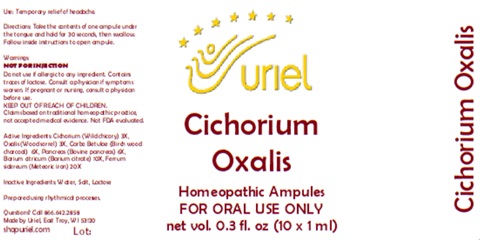 DRUG LABEL: Cichorium Oxalis
NDC: 48951-3091 | Form: LIQUID
Manufacturer: Uriel Pharmacy Inc.
Category: homeopathic | Type: HUMAN OTC DRUG LABEL
Date: 20260225

ACTIVE INGREDIENTS: CICHORIUM INTYBUS WHOLE 3 [hp_X]/1 mL; OXALIS ACETOSELLA LEAF 3 [hp_X]/1 mL; ACTIVATED CHARCOAL 6 [hp_X]/1 mL; SUS SCROFA PANCREAS 6 [hp_X]/1 mL; BARIUM CITRATE 10 [hp_X]/1 mL; IRON 20 [hp_X]/1 mL
INACTIVE INGREDIENTS: LACTOSE, UNSPECIFIED FORM; WATER; SODIUM CHLORIDE

Cichorium Oxalis

PURPOSE

Use: Temporary relief of headache.

INDICATIONS AND USAGE

FOR ORAL USE ONLY

DOSAGE AND ADMINISTRATION

Directions: Take the contents of one ampule under the tongue and hold for 30 seconds, then swallow. Follow inside instructions to open ampule.

Warnings:
NOT FOR INJECTION
Do not use if allergic to any ingredient. Contains traces of lactose. Consult a physician if symptoms worsen. If pregnant or nursing, consult a physician before use.
Claims based on traditional homeopathic practice, not accepted medical evidence. Not FDA evaluated

KEEP OUT OF REACH OF CHILDREN.

ACTIVE INGREDIENT

Active Ingredients: Cichorium (Wild chicory) 3X, Oxalis (Wood sorrel) 3X, Carbo Betulae (Birch wood charcoal) 6X, Pancreas (Bovine pancreas) 6X, Barium citricum (Barium citrate) 10X, Ferrum sidereum (Meteoric iron) 20X

Inactive Ingredients: Water, Salt, Lactose

Prepared using rhythmical processes.

QUESTIONS

Questions? Call 866.642.2858 Made by Uriel, East Troy, WI 53120 shopuriel.com Lot: